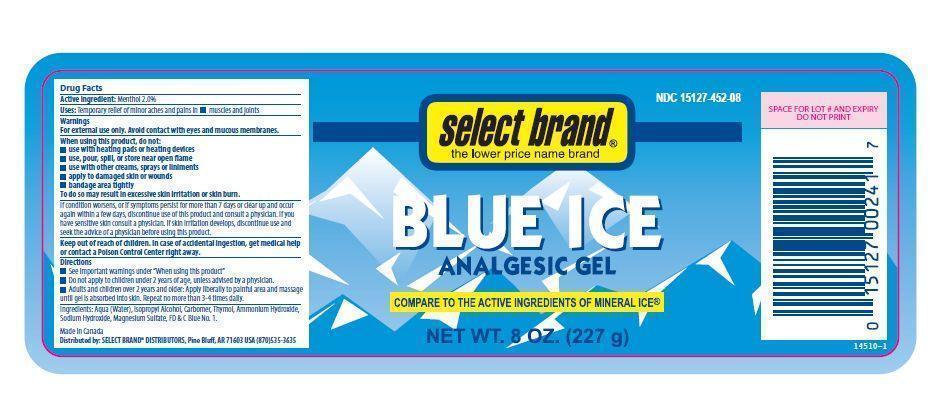 DRUG LABEL: Blue Ice Analgesic Gel
NDC: 15127-452 | Form: GEL
Manufacturer: Select Brand Distributors
Category: otc | Type: HUMAN OTC DRUG LABEL
Date: 20141007

ACTIVE INGREDIENTS: MENTHOL 2.0 g/100 g
INACTIVE INGREDIENTS: WATER 88.05 g/100 g; ISOPROPYL ALCOHOL 8.91 g/100 g; CARBOMER HOMOPOLYMER TYPE C 0.667 g/100 g; THYMOL 0.2 g/100 g; AMMONIA 0.06 g/100 g; SODIUM HYDROXIDE 0.1 g/100 g; MAGNESIUM SULFATE 0.01 g/100 g; FD&C BLUE NO. 1 0.003 g/100 g

Drug Facts

Active Ingredient

Menthol 2.0%

Uses

- Temporary relief of minor aches and pains in: muscles and joints.

Directions

- See important warnings under ''When Using This Product''.
- Do not apply to children under 2 years of age, unless advised by a physician.
- Adults and children over 2 years of age and older: Apply liberally to painful area and massage until gel is absorbed into skin. Repeat no more than 3-4 times daily.

Warnings

- For external use only.
- Avoid contact with eyes and mucus membranes.

When using this product, do not:

- use with heating pads or heating devices
- use, pour, spill or store near open flame
- use with other creams, sprays or liniments
- apply to damaged skin or wounds
- bandage area tightly

To do so may result in excessive skin irritation or skin burn.

If condition worsens, or if symptoms persist for more than 7 days or clear up and occur again within a few days, discontinue use of this product and consult a physician. If you have sensitive skin consult a physician. If skin irritation develops, discontinue use and seek the advice of a physician before using this product.

Purpose

- Analgesic.

INACTIVE INGREDIENTS

INACTIVE INGREDIENTS: WATER, ISOPROPYL ALCOHOL, CARBOMER, THYMOL, AMMONIUM HYDROXIDE, SODIUM HYDROXIDE, MAGNESIUM SULFATE, FD&C BLUE 1.

Keep out of reach of children

- In case of accidental ingestion, get medical help or contact a Poison Control Center right away.